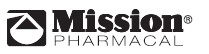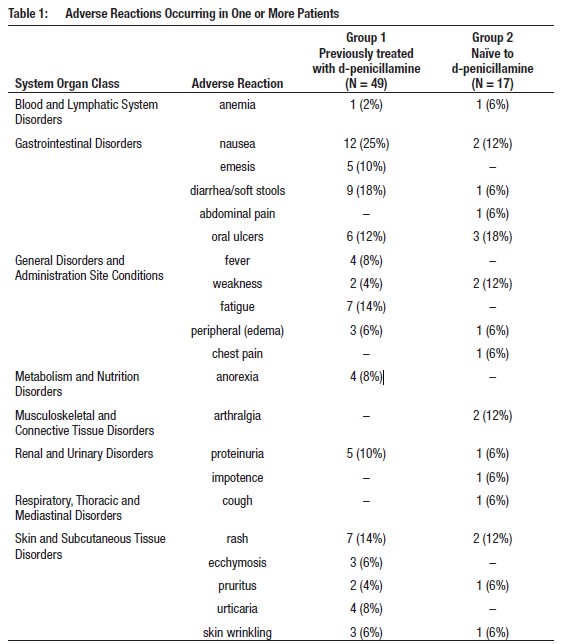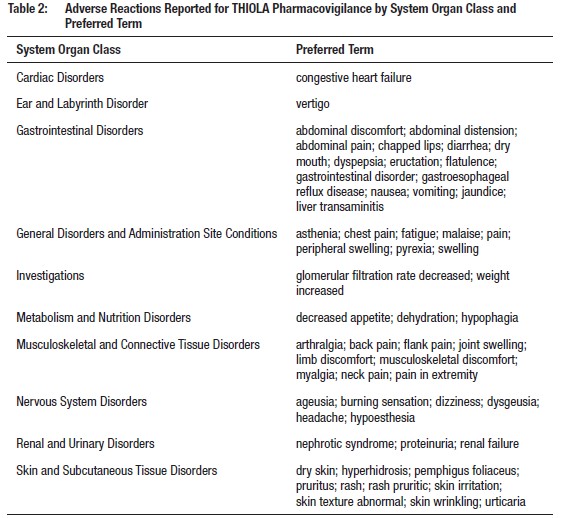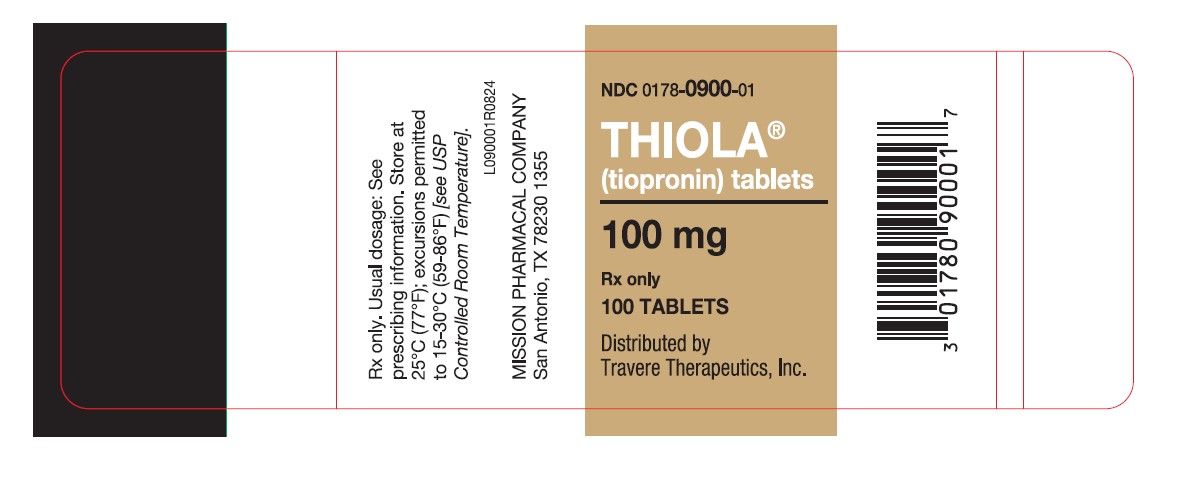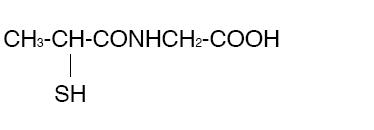 DRUG LABEL: Thiola
NDC: 0178-0900 | Form: TABLET, SUGAR COATED
Manufacturer: Mission Pharmacal Company
Category: prescription | Type: HUMAN PRESCRIPTION DRUG LABEL
Date: 20250925

ACTIVE INGREDIENTS: TIOPRONIN 100 mg/1 1
INACTIVE INGREDIENTS: SUCROSE 123 mg/1 1; CALCIUM CARBONATE 42.7 mg/1 1; LACTOSE 39 mg/1 1; DIMETHYLAMINOETHYL METHACRYLATE - BUTYL METHACRYLATE - METHYL METHACRYLATE COPOLYMER 28.8 mg/1 1; ETHYLCELLULOSES 20 mg/1 1; MAGNESIUM SILICATE 14.4 mg/1 1; MAGNESIUM STEARATE 5.4 mg/1 1; TITANIUM DIOXIDE 1.7 mg/1 1; CARNAUBA WAX 0.05 mg/1 1; FD&C RED NO. 40; ALUMINUM OXIDE; POVIDONE, UNSPECIFIED; HYDROXYPROPYL CELLULOSE (70000 WAMW)

HIGHLIGHTS OF PRESCRIBING INFORMATION
These highlights do not include all the information needed to use THIOLA® safely and effectively.
See full prescribing information for THIOLA.
THIOLA (tiopronin) tablets, for oral use
Initial U.S. Approval: 1988

1 INDICATIONS AND USAGE

--------------------------------------------INDICATIONS AND USAGE-----------------------------------------

THIOLA is a reducing and complexing thiol indicated, in combination with high fluid intake, alkali, and diet
modification, for the prevention of cystine stone formation in adults and pediatric patients 20 kg and greater
with severe homozygous cystinuria, who are not responsive to these measures alone. (1)

2 DOSAGE AND ADMINISTRATION 2.1 Recommended Dosage 2.2 Monitoring

------------------------------------------DOSAGE AND ADMINISTRATION-------------------------------------
• The recommended initial dosage in adult patients is 800 mg/day. In clinical studies, the average dosage was
about 1,000 mg/day. (2.1)
• The recommended initial dosage in pediatric patients 20 kg and greater is 15 mg/kg/day. Avoid dosages greater
than 50 mg/kg per day in pediatric patients. (2.1, 5.1, 8.4)
• Administer THIOLA in 3 divided doses at the same times each day at least one hour before or 2 hours after meals.
(2.1)
• Measure urinary cystine 1 month after initiation of THIOLA and every 3 months thereafter. (2.2)

3 DOSAGE FORMS AND STRENGTHS

-----------------------------------------DOSAGE FORMS AND STRENGTHS-----------------------------------

Tablets: 100 mg (3)

4 CONTRAINDICATIONS

----------------------------------------------CONTRAINDICATIONS------------------------------------------

• Hypersensitivity to tiopronin or any component of THIOLA (4)

5 WARNINGS AND PRECAUTIONS 5.1 Proteinuria 5.2 Hypersensitivity Reactions

------------------------------------------WARNINGS AND PRECAUTIONS-------------------------------------

• Proteinuria, including nephrotic syndrome, and membranous nephropathy, has been reported with tiopronin use.
Pediatric patients receiving greater than 50 mg/kg of tiopronin per day may be at increased risk for proteinuria.
(2.1, 5.1, 8.4)
• Hypersensitivity reactions have been reported during tiopronin treatment. (4, 5.2)

6 ADVERSE REACTIONS 6.1 Clinical Trials Experience 6.2 Postmarketing Experience

---------------------------------------------ADVERSE REACTIONS-------------------------------------------

Most common adverse reactions (≥10%) are nausea, diarrhea or soft stools, oral ulcers, rash, fatigue, fever,
arthralgia, proteinuria, and emesis. (6)
To report SUSPECTED ADVERSE REACTIONS, contact Mission Pharmacal Company at toll-free phone #
1-800-298-1087 or FDA at 1-800-FDA-1088 or www.fda.gov/medwatch.

8 USE IN SPECIFIC POPULATIONS 8.1 Pregnancy 8.2 Lactation 8.4 Pediatric Use 8.5 Geriatric Use

-----------------------------------------USE IN SPECIFIC POPULATIONS--------------------------------------

• Lactation: Breastfeeding is not recommended. (8.2)
• Geriatric: Choose dose carefully and monitor renal function in the elderly. (8.5)

See 17 for PATIENT COUNSELING INFORMATION.

Revised: 01/2021

FULL PRESCRIBING INFORMATION

1 INDICATIONS AND USAGE

THIOLA is indicated, in combination with high fluid intake, alkali, and diet modification, for the prevention of
cystine stone formation in adults and pediatric patients 20 kg and greater with severe homozygous cystinuria,
who are not responsive to these measures alone.

2 DOSAGE AND ADMINISTRATION 2.1 Recommended Dosage 2.2 Monitoring

2.1 Recommended Dosage

Adults: The recommended initial dosage in adult patients is 800 mg/day. In clinical studies, the average
dosage was about 1,000 mg/day.

Pediatrics: The recommended initial dosage in pediatric patients weighing 20 kg and greater is 15 mg/kg/day.
Avoid dosages greater than 50 mg/kg per day in pediatric patients [see Warnings and Precautions (5.1), Use in
Specific Populations (8.4)].

Administer THIOLA in 3 divided doses at the same times each day at least one hour before or 2 hours after
meals.

Consider starting THIOLA at a lower dosage in patients with history of severe toxicity to d-penicillamine.

2.2 Monitoring
Measure urinary cystine 1 month after starting THIOLA and every 3 months thereafter. Adjust THIOLA dosage
to maintain urinary cystine concentration less than 250 mg/L.

Assess for proteinuria before treatment and every 3 to 6 months during treatment [see Warnings and
Precautions (5.1)].

Discontinue THIOLA in patients who develop proteinuria, and monitor urinary protein and renal function.
Consider restarting THIOLA treatment at a lower dosage after resolution of proteinuria.

3 DOSAGE FORMS AND STRENGTHS

Tablets for oral use:
100 mg tablets: round, white and imprinted in red with “M” on one side

4 CONTRAINDICATIONS

THIOLA is contraindicated in patients with hypersensitivity to tiopronin or any other components of THIOLA
[see Warnings and Precautions (5.2)].

5 WARNINGS AND PRECAUTIONS 5.1 Proteinuria 5.2 Hypersensitivity Reactions

5.1 Proteinuria
Proteinuria, including nephrotic syndrome, and membranous nephropathy, have been reported with tiopronin
use. Pediatric patients receiving greater than 50 mg/kg of tiopronin per day may be at increased risk for
proteinuria [see Dosage and Administration (2.2), Adverse Reactions (6.1, 6.2), Use in Specific Populations
(8.4)]. Monitor patients for the development of proteinuria and discontinue therapy in patients who develop
proteinuria [see Dosage and Administration (2.2)].

5.2 Hypersensitivity Reactions
Hypersensitivity reactions (drug fever, rash, fever, arthralgia and lymphadenopathy) have been reported [see
Contraindications (4)].

6 ADVERSE REACTIONS 6.1 Clinical Trials Experience 6.2 Postmarketing Experience

The following adverse reactions are discussed in greater detail in other sections of the labeling:
• Proteinuria [see Warnings and Precautions (5.1)]
• Hypersensitivity [see Warnings and Precautions (5.2)]

6.1 Clinical Trials Experience
Because clinical trials are conducted under widely varying conditions, the adverse reaction rates observed in
the clinical trials of the drug cannot be directly compared to rates in the clinical trials of another drug and may
not reflect the rates observed in practice.

Adverse reactions occurring at an incidence of ≥5% in an uncontrolled trial in 66 patients with cystinuria
age 9 to 68 years are shown in the table below. Patients in group 1 had previously been treated with
d-penicillamine; those in group 2 had not. Of those patients who had stopped taking d-penicillamine due to
toxicity (34 out of 49 patients in group 1), 22 were able to continue treatment with THIOLA. In those without
prior history of d-penicillamine treatment, 6% developed reactions of sufficient severity to require THIOLA
withdrawal.
Table 1 presents adverse reactions ≥5% in either treatment group occurring in this trial.

Taste Disturbance
A reduction in taste perception may develop. It is believed to be the result of chelation of trace metals by
tiopronin. Hypogeusia is often self-limited.

6.2 Postmarketing Experience
Adverse reactions have been reported from the literature, as well as during post-approval use of THIOLA.
Because the post-approval reactions are reported voluntarily from a population of uncertain size, it is not
always possible to reliably estimate their frequency or establish a causal relationship to THIOLA exposure.
Adverse reactions reported during the postmarketing use of THIOLA are listed by body system in Table 2.

8 USE IN SPECIFIC POPULATIONS 8.1 Pregnancy 8.2 Lactation 8.4 Pediatric Use 8.5 Geriatric Use

8.1 Pregnancy
Risk Summary
Available published case report data with tiopronin have not identified a drug-associated risk for major birth
defects, miscarriage, or adverse maternal or fetal outcomes. Renal stones in pregnancy may result in adverse
pregnancy outcomes (see Clinical Considerations). In animal reproduction studies, there were no adverse
developmental outcomes with oral administration of tiopronin to pregnant mice and rats during organogenesis
at doses up to 2 times a 2 grams/day human dose (based on mg/m^2). The estimated background risk of major
birth defects and miscarriage for the indicated population is unknown. All pregnancies have a background
risk of birth defect, loss, or other adverse outcomes. In the U.S. general population, the estimated background
risk of major birth defects and miscarriage in clinically recognized pregnancies are 2% to 4% and 15% to
20%, respectively.
Clinical Considerations
Disease-associated maternal and/or embryo/fetal risk
Renal stones in pregnancy may increase the risk of adverse pregnancy outcomes, such as preterm birth and
low birth weight.
Data
Animal Data
No findings of fetal malformations could be attributed to the drug in reproduction studies in mice and rats at
doses up to 2 times the highest recommended human dose of 2 grams/day (based on mg/m^2).
8.2 Lactation
Risk Summary
There are no data on the presence of tiopronin in either human or animal milk or on the effects of the
breastfed child. A published study suggests that tiopronin may suppress milk production. Because of the
potential for serious adverse reactions, including nephrotic syndrome, advise patients that breastfeeding is not
recommended during treatment with THIOLA.
8.4 Pediatric Use
THIOLA is indicated in pediatric patients weighing 20 kg or more with severe homozygous cystinuria, in
combination with high fluid intake, alkali, and diet modification, for the prevention of cystine stone formation
who are not responsive to these measures alone. This indication is based on safety and efficacy data from a
trial in patients 9 years to 68 years of age and clinical experience. Proteinuria, including nephrotic syndrome,
has been reported in pediatric patients. Pediatric patients receiving greater than 50 mg/kg tiopronin per day
may be at greater risk [see Dosage and Administration (2.1, 2.2), Warnings and Precautions (5.1) and Adverse
Reactions (6.1)].
THIOLA tablets are not approved for use in pediatric patients weighing less than 20 kg or in pediatric patients
unable to swallow tablets [see Recommended Dosage (2.1)].
8.5 Geriatric Use
This drug is known to be substantially excreted by the kidney, and the risk of adverse reactions to this drug
may be greater in patients with impaired renal function. Because elderly patients are more likely to have
decreased renal function, care should be taken in dose selection, and it may be useful to monitor renal
function.

10 OVERDOSAGE

There is no information on overdosage with tiopronin.

11 DESCRIPTION

THIOLA (tiopronin) immediate-release tablets are a reducing and cystine-binding thiol drug (CBTD) for oral
use. Tiopronin is N-(2-Mercaptopropionyl) glycine and has the following structure:

Tiopronin has the empirical formula C5H9NO3S and a molecular weight of 163.20. In this drug product tiopronin
exists as a dl racemic mixture.

Tiopronin is a white crystalline powder, which is freely soluble in water.
Each THIOLA tablet contains 100 mg of tiopronin. The inactive ingredients in THIOLA tablets include calcium
carbonate, carnauba wax, ethyl cellulose, dimethylaminoethyl methacrylate: butyl methacrylate: methyl
methacrylate copolymer (Eudragit E 100), hydroxy-propyl cellulose, lactose monohydrate, magnesium
stearate, povidone, sugar, talc, titanium dioxide.

12 CLINICAL PHARMACOLOGY 12.1 Mechanism of Action 12.2 Pharmacodynamics 12.3 Pharmacokinetics

12.1 Mechanism of Action

The goal of therapy is to reduce urinary cystine concentration below its solubility limit. Tiopronin is an active
reducing agent which undergoes thiol-disulfide exchange with cystine to form a mixed disulfide of tiopronincysteine.
From this reaction, a water-soluble mixed disulfide is formed and the amount of sparingly soluble
cystine is reduced.
12.2 Pharmacodynamics
The decrement in urinary cystine produced by tiopronin is generally proportional to the dose. A reduction in
urinary cystine of 250-350 mg/day at tiopronin dosage of 1 g/day, and a decline of approximately 500 mg/day
at a dosage of 2 g/day, might be expected. Tiopronin has a rapid onset and offset of action, showing a fall in
cystine excretion on the first day of administration and a rise on the first day of drug withdrawal.
12.3 Pharmacokinetics
Absorption
THIOLA Tablets
When THIOLA single doses were given to fasted healthy subjects (n = 39), the median time to peak plasma
level (Tmax) was 1 (range: 0.5 to 2.1) hours.
Elimination

Excretion
When tiopronin is given orally, up to 48% of dose appears in urine during the first 4 hours and up to 78% by
72 hours.

13 NONCLINICAL TOXICOLOGY 13.1 Carcinogenesis, Mutagenesis, Impairment of Fertility

13.1 Carcinogenesis, Mutagenesis, Impairment of Fertility
Carcinogenesis
Long-term carcinogenicity studies in animals have not been performed.
Mutagenesis
Tiopronin was not genotoxic in the chromosomal aberration, sister chromatid exchange, and in vivo
micronucleus assays.
Impairment of Fertility
High doses of tiopronin in experimental animals have been shown to interfere with maintenance of pregnancy
and viability of the fetus. In 2 published male fertility studies in rats, tiopronin at 20 mg/kg/day intramuscular
(IM) for 60 days induced reductions in testis, epididymis, vas deferens, and accessory sex glands weights and
in the count and motility of cauda epididymal sperm.

16 HOW SUPPLIED/STORAGE AND HANDLING

100 mg round, white, immediate-release tablet imprinted in red with “M” on one side and blank on the other
side: Bottles of 100 NDC 0178-0900-01.
Store at 25°C (77°F); excursions permitted to 15-30°C (59-86°F) [see USP Controlled Room Temperature].

17 PATIENT COUNSELING INFORMATION

Lactation

Advise women that breastfeeding is not recommended during treatment with THIOLA [see Use in Specific
Populations (8.2)].

PACKAGE LABEL

Manufactured and packaged by Mission Pharmacal Company, San Antonio, TX 78230 1355
Distributed by Travere Therapeutics, Inc., San Diego, CA 92130
Copyright © 2024 Mission Pharmacal Company. All rights reserved.
L090201R0824
THL_T13758R0824